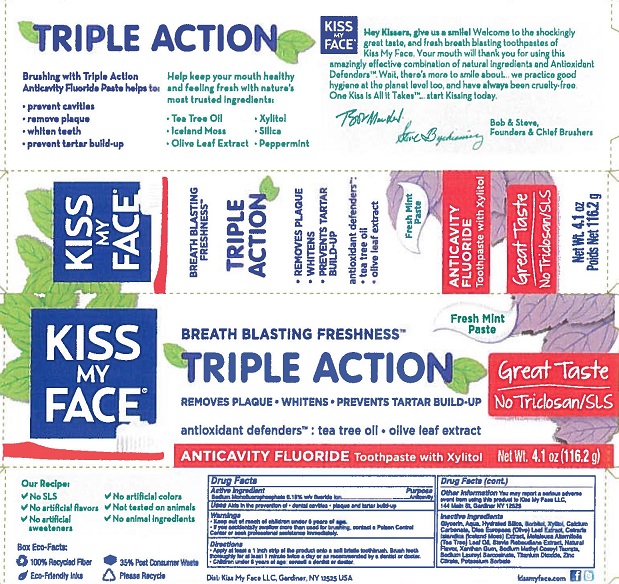 DRUG LABEL: Kiss My Face
NDC: 65364-402 | Form: PASTE, DENTIFRICE
Manufacturer: Kiss My Face, LLC
Category: otc | Type: HUMAN OTC DRUG LABEL
Date: 20190220

ACTIVE INGREDIENTS: SODIUM MONOFLUOROPHOSPHATE 0.76 g/100 g
INACTIVE INGREDIENTS: SORBITOL; WATER; TEA TREE OIL; OLEA EUROPAEA LEAF; SODIUM METHYL COCOYL TAURATE; SODIUM LAUROYL SARCOSINATE; XANTHAN GUM; STEVIA REBAUDIUNA LEAF; CETRARIA ISLANDICA SUBSP. ISLANDICA; POTASSIUM SORBATE; GLYCERIN; HYDRATED SILICA; XYLITOL; CALCIUM CARBONATE; ZINC CITRATE; TITANIUM DIOXIDE

Kiss My Face Triple Action Toothpaste Fresh Mint

Drug Facts

Active ingredient

Sodium Monofluorphosphate 0.15% w/w fluoride ion

Purpose

Anticavity

Uses

Aids in the prevention of

- dental cavities
- plaque and tartar build-up

Warnings

- Keep out of reach of children under 6 years of age.
- If you accidentally swallow more than used for brushing, contact a Poison Control Center or seek professional assistance immediately.

Directions

- Apply at least a 1 inch strip of the product onto a soft bristle toothbrush. Brush teeth thoroughly for at least 1 minute twice a day or as recommended by a dentist or doctor.
- Children under 6 years of age: consult a dentist or doctor

Other information

You may report a serious adverse event from using this product to Kiss My Face, LLC, 144 Main Street, Gardiner, NY 12525.

INACTIVE INGREDIENT

Inactive ingredients Glycerin, Aqua, Hydrated Silica, Sorbitol, Xylitol, Calcium Carbonate, Olea Europaea (Olive) Leaf Extract, Cetraria Islandica (Iceland Moss) Extract, Melaleuca Alternifolia (Tea Tree) Leaf Oil, Stevia Rebaudiana Extract, Natural Flavor, Xanthan Gum, Sodium Methyl Cocoyl Taurate, Sodium Lauroyl Sarcosinate, Titanium Dioxide, Zinc Citrate, Potassium Sorbate

Dist. Kiss My Face LLC, Gardiner, NY 12525 USA

PACKAGE LABEL

KISS MY FACE®

BREATH BLASTING FRESHNESS™

TRIPLE ACTION ANTICAVITY FLUORIDE Toothpaste with Xylitol

REMOVES PLAQUE • WHITENS • PREVENTS TARTAR BUILD-UP

Fresh Mint Paste

Great Taste - No Triclosan/SLS

antioxidant defenders™: tea tree oil • olive leaf extract

Net Wt.. 4.1 oz (116.2 g)